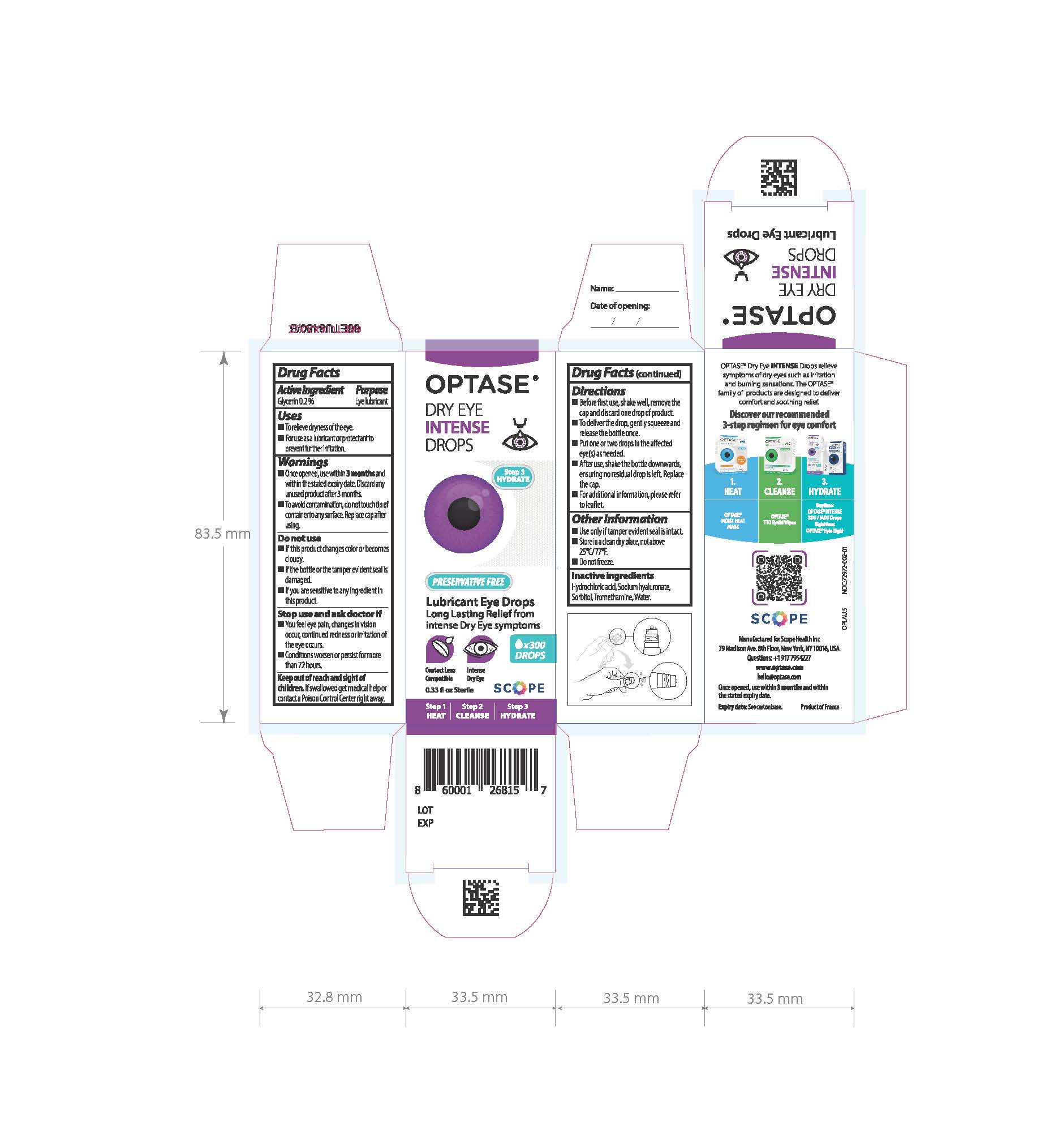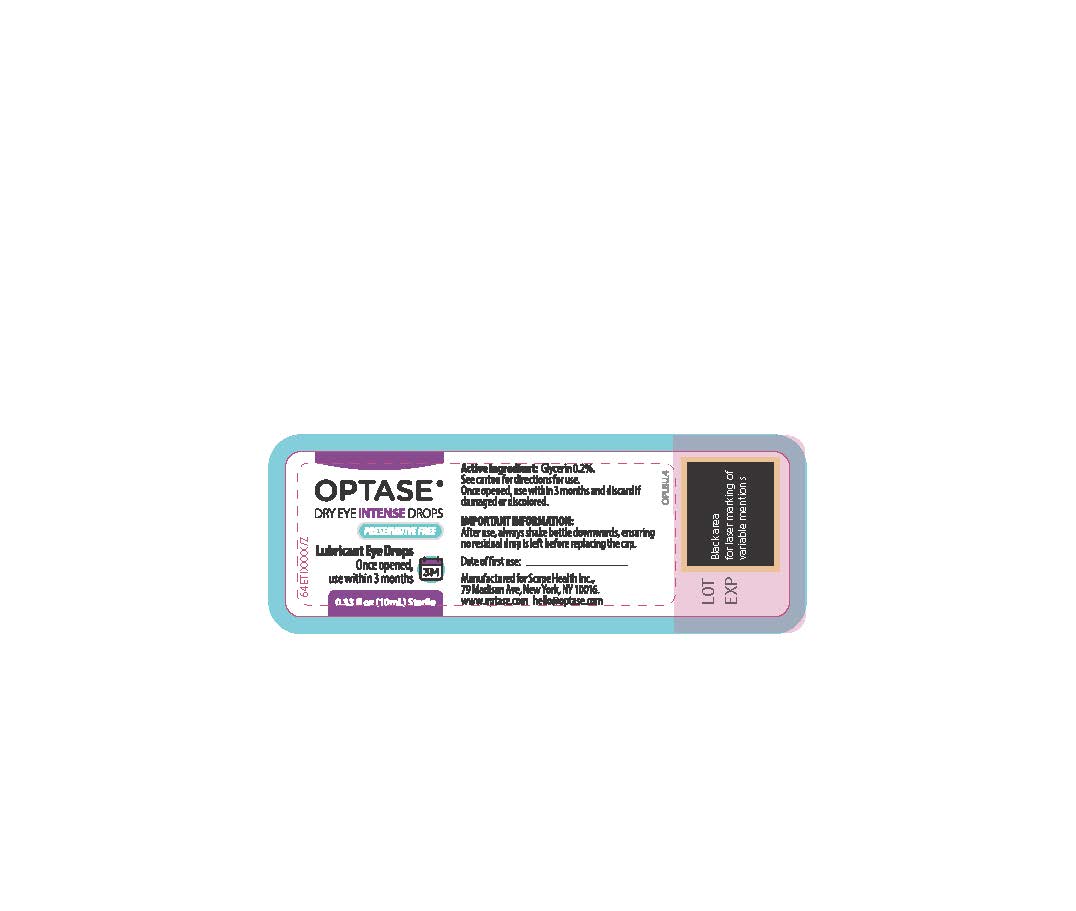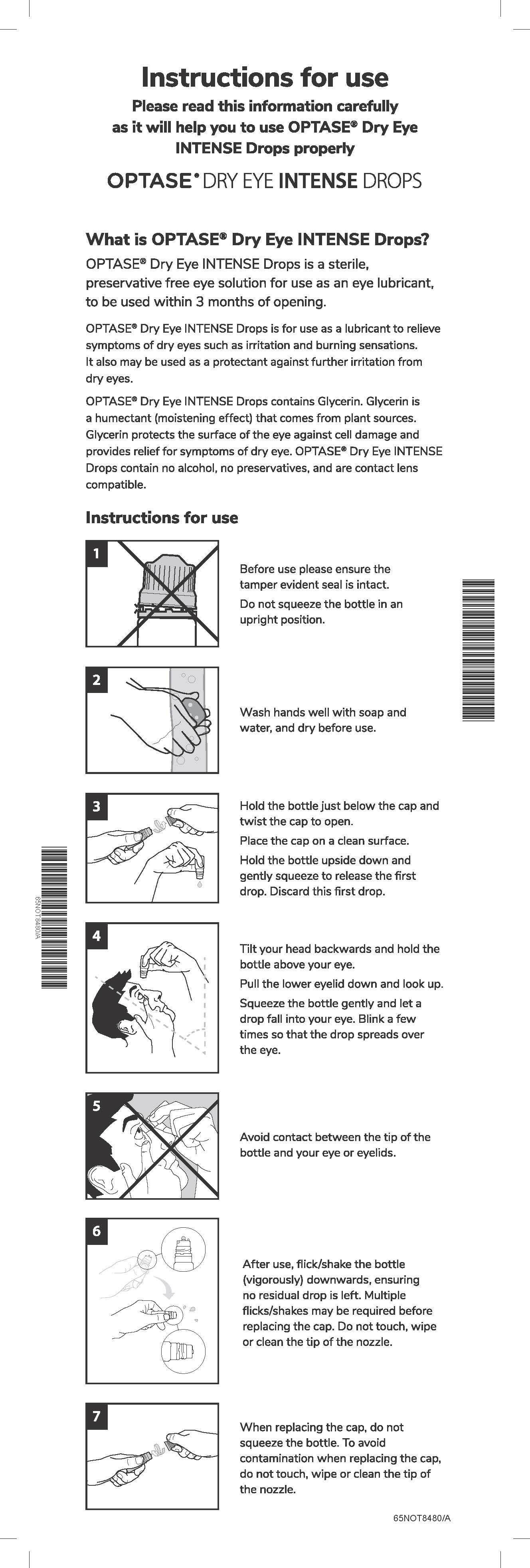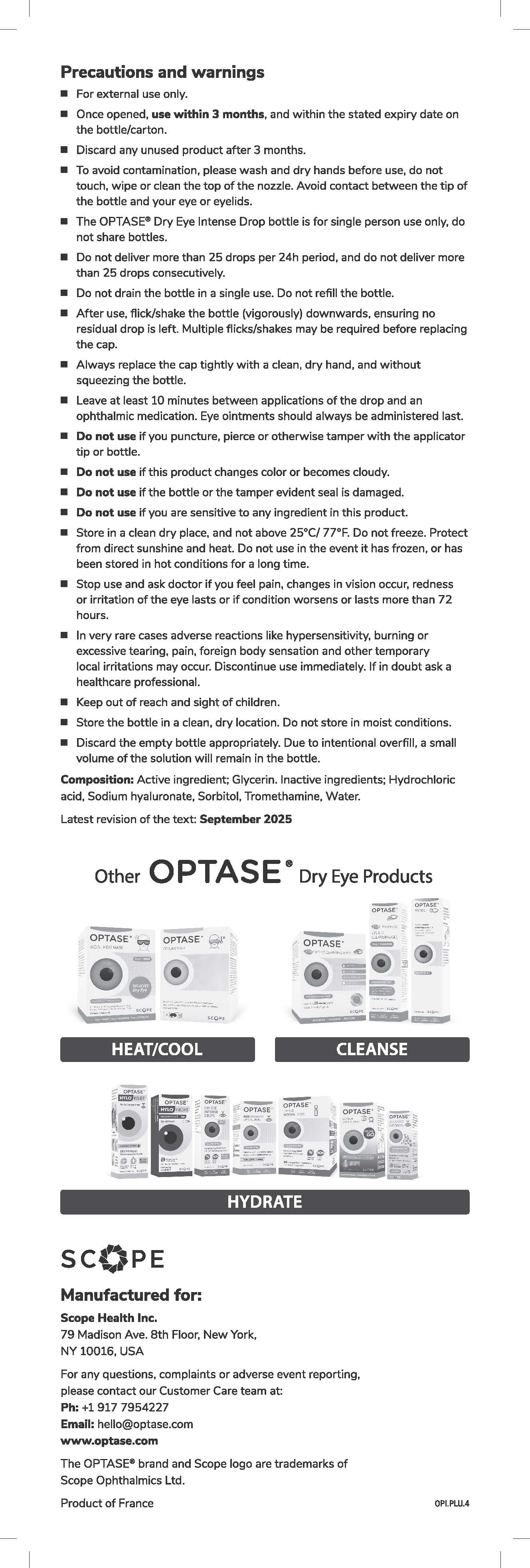 DRUG LABEL: Optase
NDC: 72972-002 | Form: SOLUTION/ DROPS
Manufacturer: Scope Health Inc
Category: otc | Type: HUMAN OTC DRUG LABEL
Date: 20260130

ACTIVE INGREDIENTS: GLYCERIN 2 mg/1 mL
INACTIVE INGREDIENTS: HYALURONATE SODIUM; HYDROCHLORIC ACID; WATER; TROMETHAMINE; SORBITOL

Optase Dry Eye Intense Drops

Inactive ingredients
Hydrochloric acid, Sodium hyaluronate, Sorbitol,
Tromethamine, Water.

Warnings
• For external use only.
• Once opened, use within 3 months and within the
stated expiry date.
• Discard any unused product after 3 months.
• To avoid contamination do not touch, wipe or clean
the tip of the nozzle. Replace cap tightly after using.
Do not use
• If this product changes color or becomes cloudy.
• If the bottle or the tamper evident seal is damaged.
• If you puncture, pierce or otherwise tamper with the
applicator tip or bottle.
• If you are sensitive to any ingredient in this product.
When using this product
• To avoid contamination do not touch, wipe or clean
the tip of the nozzle.
• Do not squeeze the bottle when removing and
replacing the cap.
Stop use and ask doctor if
• You feel eye pain, changes in vision occur, continued
redness or irritation of the eye occurs.
• Conditions worsen or persist for more than 72 hours.
Keep out of reach and sight of children.
If swallowed get medical help or contact a
Poison Control Center right away.

Uses
• To relieve dryness of the eye.
• For use as a lubricant or protectant to prevent
further irritation.

Directions
• Shake well before use.
• Before first use, remove the cap, hold the bottle
upside down and discard one drop of product.
• To deliver the drop, gently squeeze and release
the bottle once.
• Put one or two drops in the affected eye(s) as needed.
• After use, flick/shake the bottle (vigorously)
downwards, ensuring no residual drop is left.
Multiple flicks/shakes may be required before
replacing the cap. See diagram 1 below.
• Do not deliver more than 25 drops per 24h period,
and do not deliver more than 25 drops consecutively.
• For additional information, please refer to leaflet.

ACTIVE INGREDIENT

Glycerin 0.2 %

PURPOSE

Eye Lubricant

Keep out of reach and sight of children.
If swallowed get medical help or contact a
Poison Control Center right away.